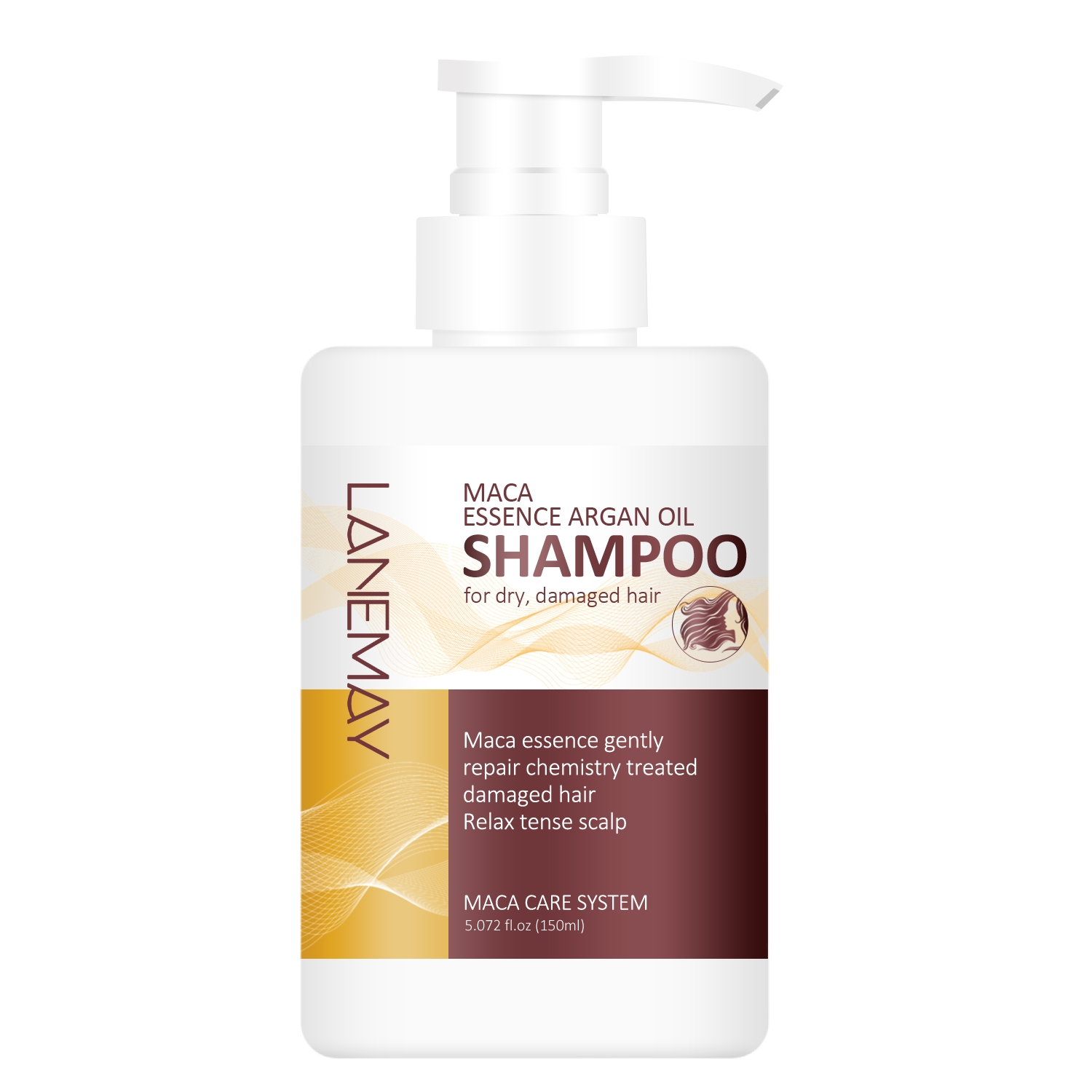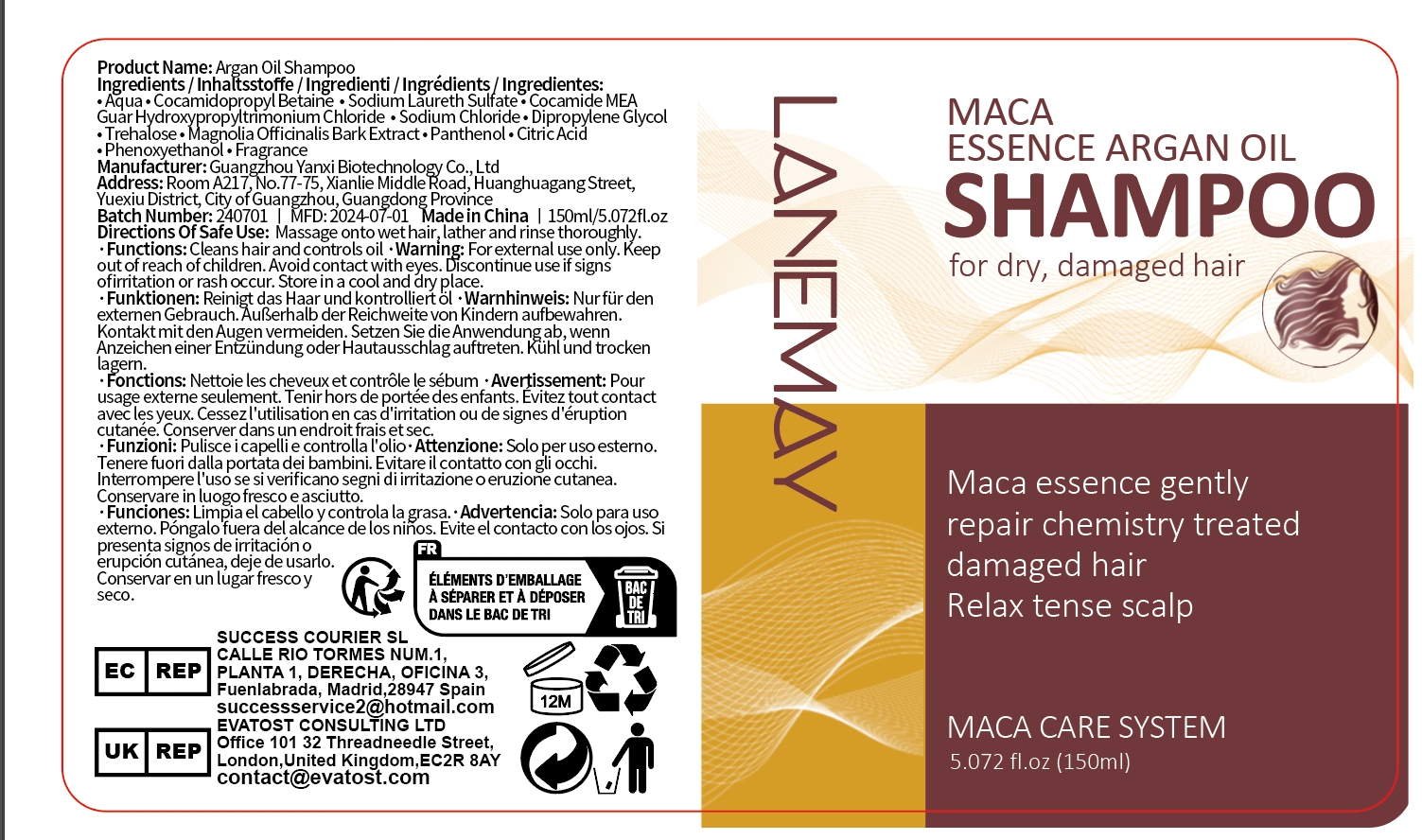 DRUG LABEL: Argan OilShampoo
NDC: 84025-073 | Form: SHAMPOO
Manufacturer: Guangzhou Yanxi Biotechnology Co.. Ltd
Category: otc | Type: HUMAN OTC DRUG LABEL
Date: 20240720

ACTIVE INGREDIENTS: COCAMIDOPROPYL BETAINE 5 mg/150 mL; DIPROPYLENE GLYCOL 3 mg/150 mL
INACTIVE INGREDIENTS: WATER

DOSAGE AND ADMINISTRATION

Cleanses and moisturizes hair and scalp

WARNINGS

Keep out of children

INACTIVE INGREDIENT

Aqua

INDICATIONS AND USAGE

hair care

keep out of children

PURPOSE

Repair and moisturize your scalp